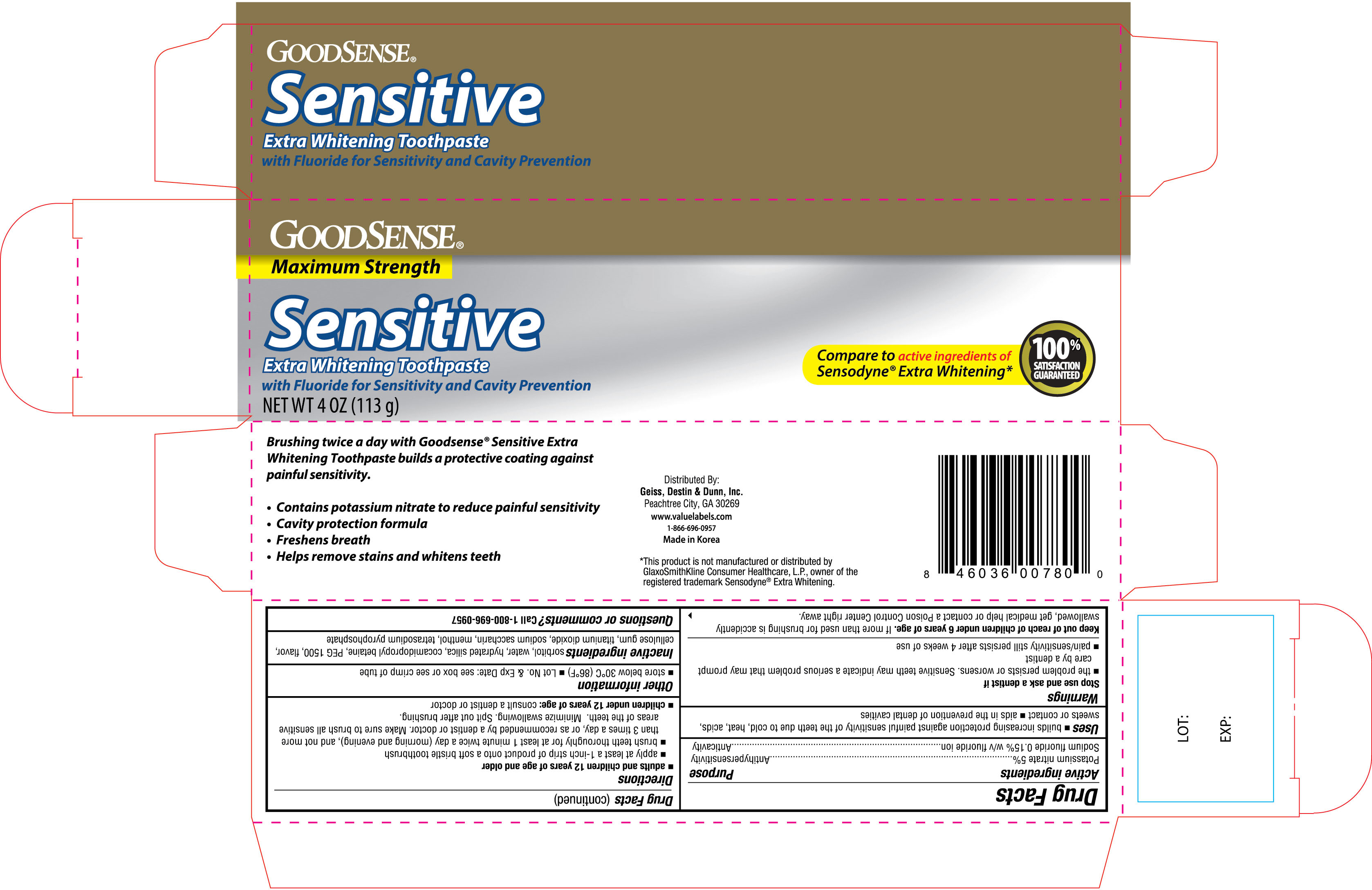 DRUG LABEL: Goodsense Sensitive Extra Whitening
NDC: 50804-780 | Form: PASTE
Manufacturer: Geiss, Destin & Dunn, Inc.
Category: otc | Type: HUMAN OTC DRUG LABEL
Date: 20171212

ACTIVE INGREDIENTS: POTASSIUM NITRATE 50 mg/1 g; SODIUM FLUORIDE 1.5 mg/1 g
INACTIVE INGREDIENTS: SORBITOL; WATER; HYDRATED SILICA; COCAMIDOPROPYL BETAINE; POLYETHYLENE GLYCOL 1500; TITANIUM DIOXIDE; MENTHOL

Goodsense Sensitive Toothpaste Extra Whitening 4 oz NBE Sensodyne

Active ingredients Purpose

Potassium nitrate 5%........................................ Antihypersensitivity

Sodium fluoride 0.15% w/v fluoride ion..............................Anticavity

Uses

- builds increasing protection against painful sensitivity of the teeth due to cold, heat, acids, sweets or contact
- aids in the prevention of dental cavities

Warnings

Stop use and ask a dentist if

- the problem persists or worsens. Sensitive teeth may indicate a serious problem that may prompt care by a dentist
- pain/sensitivty still persists after 4 weeks of use

Keep out of reach of children under 6 years of age. If more than used for brushing is accidently swallowed, get medical help or contact a Poison Control Center right away.

Directions

- adults and children 12 years of age and older
- appy at least 1-inch strip of product onto a soft bristle toothbrush
- brush teeth thoroughly for at least 1 minute twice a day (morning and evening), and not more than 3 times a day, or as recommended by a dentist or doctor. Make sure to brush all sensitive areas of the teeth. Minimize swallowing. Spit out after brushing.
- children under 12 years of age: consult a dentist or doctor

Other information

- store below 30°C (86°F)
- Lot No. & Exp. Date: see box or see crimp of tube

INACTIVE INGREDIENT

Inactive ingredients sorbitol, water, hydrated silica, cocamidopropyl betaine, PEG 1500, flavor, cellulose gum, titanium dioxide, sodium saccharin, menthol, tetrasodium pyrophosphate

DOSAGE AND ADMINISTRATION

Distributed by:

Geiss, Destin & Dunn, Inc.

Peachtree City, GA 30269

Made in Korea